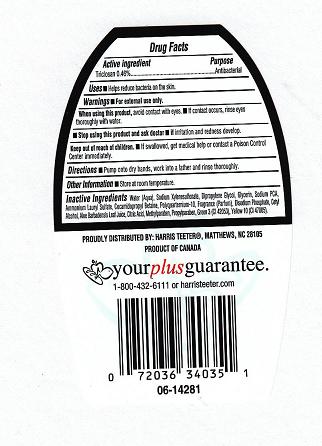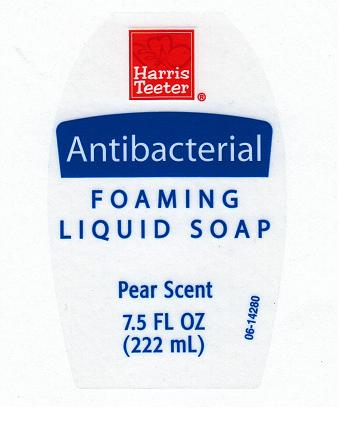 DRUG LABEL: ANTIBACTERIAL FOAMING 
NDC: 72036-163 | Form: SOAP
Manufacturer: HARRIS TEETER
Category: otc | Type: HUMAN OTC DRUG LABEL
Date: 20101108

ACTIVE INGREDIENTS: TRICLOSAN 0.46 mL/100 mL
INACTIVE INGREDIENTS: WATER; SODIUM POLYSTYRENE SULFONATE; DIPROPYLENE GLYCOL; GLYCERIN; SODIUM PYRROLIDONE CARBOXYLATE; AMMONIUM LAURYL SULFATE; COCAMIDOPROPYL BETAINE; POLYQUATERNIUM-10 (400 CPS AT 2%); SODIUM PHOSPHATE, DIBASIC, DIHYDRATE; CETYL ALCOHOL; ALOE VERA LEAF; CITRIC ACID MONOHYDRATE; METHYLPARABEN; PROPYLPARABEN; FD&C GREEN NO. 3; D&C YELLOW NO. 10

DRUG FACTS - BACK PANEL

Active Ingredient

Triclosan 0.46%

Purpose

Antibacterial

Uses

Helps reduce bacteria on the skin.

Warnings

For external use only

When using this product

avoid contact with eyes. If contact occurs, rinse eyes thoroughly with water.

Stop using this product and ask doctor if

irritation and redness develop.

Keep out of reach of children

If swallowed, get medical help or contact a poison control center immediately.

Directions

Pump onto dry hands, work into lather and rinse thoroughly.

Other information

Store at room temperature

Inactive ingredients

Water (Aqua), Sodium Xylenesulfonate, Dipropylene Glycol, Glycerin, Sodium PCA, Ammonium Lauryl Sulfate, Cocamidopropyl Betaine, Polyquaternium-10, Fragrance (Parfum), Disodium Phosphate, Cetyl Alcohol, Aloe Barbadensis Leaf Juice, Citric Acid, Methylparaben, Propylparaben, Green 3 (CI 42053). Yellow 10 (CI 47005).

PACKAGE LABEL

htf.jpg

htb.jpg